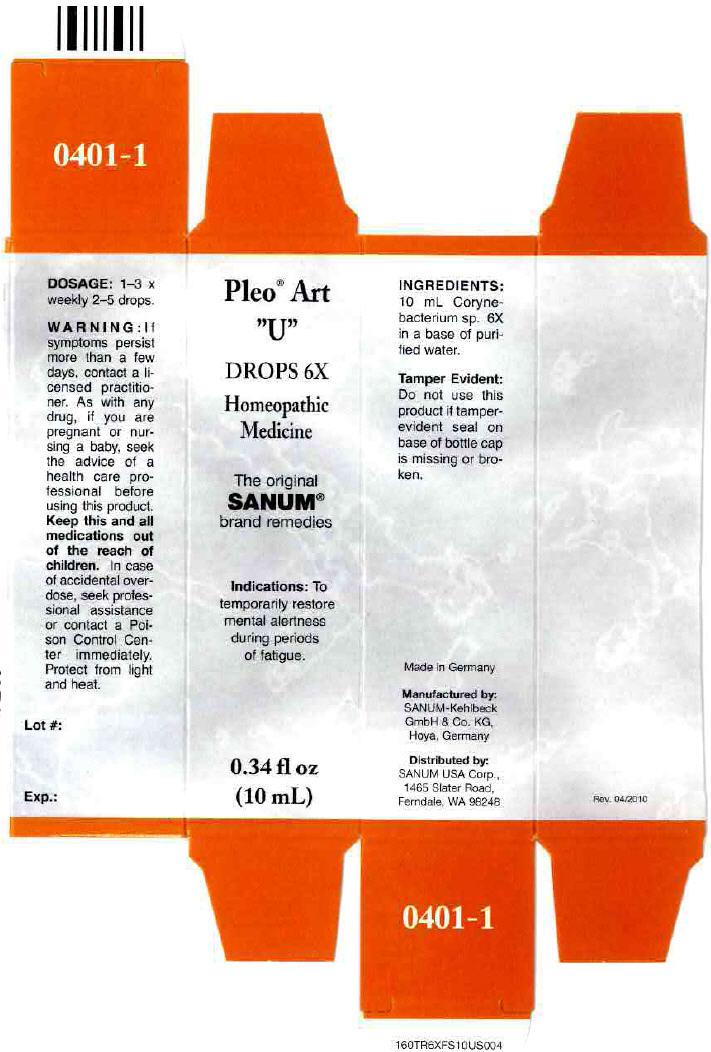 DRUG LABEL: Pleo Art U
NDC: 60681-0401 | Form: SOLUTION/ DROPS
Manufacturer: Sanum Kehlbeck GmbH & Co. KG
Category: homeopathic | Type: HUMAN OTC DRUG LABEL
Date: 20120307

ACTIVE INGREDIENTS: Brevibacterium Stationis 6 [hp_X]/10 mL
INACTIVE INGREDIENTS: water

Pleo™ Art "U"
DROPS 6X

Homeopathic Medicine

0.34 fl oz
(10 mL)

Indications

PURPOSE

To temporarily restore mental alertness during periods of fatigue

INGREDIENTS

INACTIVE INGREDIENT

10 mL Corynebacterium sp. 6X in a base of purified water.

Tamper Evident

Do not use this product if the plastic band at base of bottle cup is broken.

DOSAGE

1–3 × weekly 2–5 drops.

WARNING

If symptoms persist more than a few days, contact a licensed practitioner. As with any drug, if you are pregnant or nursing a baby, seek the advice of a health care professional before using this product.

KEEP OUT OF REACH OF CHILDREN

Keep this and all medications out of the reach of children. In case of accidental overdose, seek professional assistance or contact a Poison Control Center immediataly.

STORAGE AND HANDLING

Protect from light and heat.

Made in Germany.

Distributed by:
SANUM USA Corp.
1465 Slater Road
Ferndale, WA 98248

Manufactured By:
Sanum-Kehlbeck
GmbH & Co. KG

Rev. 8/2001

PRINCIPAL DISPLAY PANEL - 10 mL Bottle, Dropper Carton

Pleo® Art
"U"
DROPS 6X

Homeopathic
Medicine

The original
SANUM®
brand remedies

Indications: To
temporarily restore
mental alertness
during periods
of fatigue.

0.34 fl oz
(10 mL)